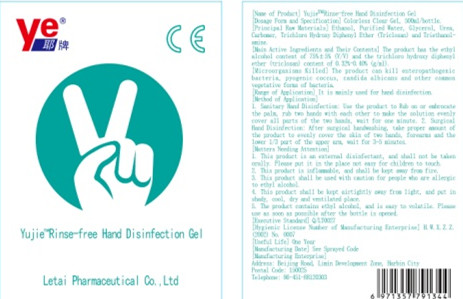 DRUG LABEL: YujieTM Rinse-free Hand Disinfection Gel
NDC: 52716-002 | Form: GEL
Manufacturer: Letai Pharmaceutical Co., Ltd.
Category: otc | Type: HUMAN OTC DRUG LABEL
Date: 20200413

ACTIVE INGREDIENTS: ALCOHOL 375 mL/500 mL
INACTIVE INGREDIENTS: WATER; GLYCERIN; CARBOMER HOMOPOLYMER, UNSPECIFIED TYPE; UREA; TROLAMINE

DOSAGE FORMS AND STRENGTHS

Proper amount

INACTIVE INGREDIENT

Purified Water

Glycerol

Urea

Carbomer

Triethanolamine

INDICATIONS AND USAGE

1. Hygienic hand disinfection: Take an appropriate amount of this product to the palm of your hand, rub your hands together to evenly coat each part. Play for 1 minute.
2.Surgical hand disinfection: After surgical hand washing, take an appropriate amount of this product and evenly spread it on both

hands. The skin on the lower third of the forearm and upper arm. Take 3 to 5 minutes.

ACTIVE INGREDIENT

alcohol

keep out of children

PURPOSE

No need to use water for cleaning and disinfecting hands.

WARNINGS

1. This product is a disinfectant for external use and should not be taken orally. Keep out of reach of children.
2 This product is flammable and should be kept away from fire.
3. Use with caution for those who are allergic to ethanol.
4. Intimate. Store away from light and store in a cool place. Dry. Hand wind.
5. This product contains ethanol and is volatile. Please use as soon as possible after opening the bottle.

DOSAGE AND ADMINISTRATION

1. This product is a disinfectant for external use and should not be taken orally. Keep out of the reach of children.
2. This product is flammable and should be kept away from fire.
3. Use with caution for those who are allergic to ethanol.
4. Keep tightly closed, protected from light, and store in a cool, dry and ventilated place.
5. This product contains ethanol and is volatile. Please use it as soon as possible after opening the bottle.